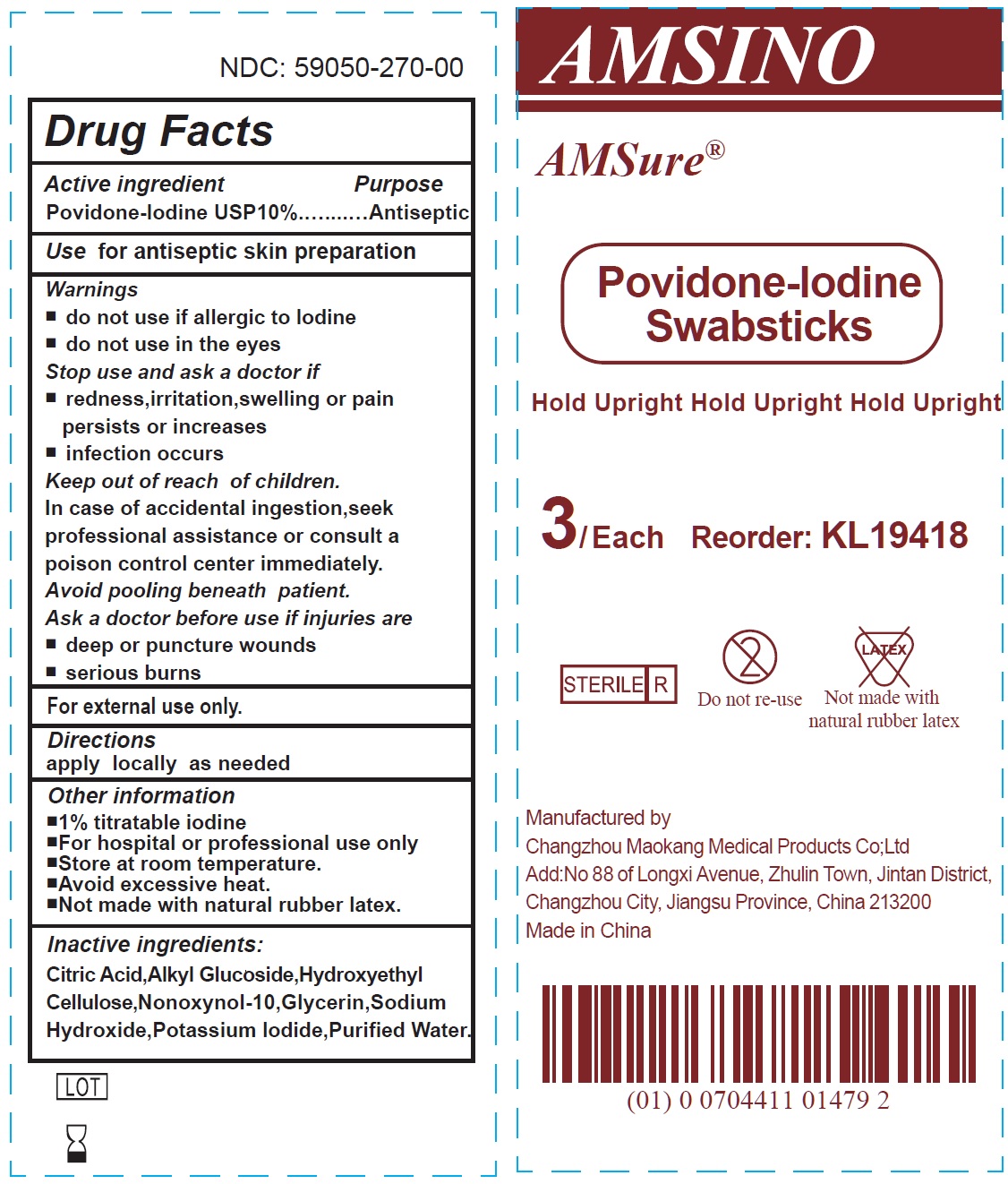 DRUG LABEL: Povidone Iodine Swabsticks
NDC: 59050-270 | Form: SOLUTION
Manufacturer: Changzhou Maokang Medical Products Co., Ltd
Category: otc | Type: HUMAN OTC DRUG LABEL
Date: 20241121

ACTIVE INGREDIENTS: POVIDONE-IODINE 100 mg/1 g
INACTIVE INGREDIENTS: CITRIC ACID MONOHYDRATE; HYDROXYETHYL CELLULOSE, UNSPECIFIED; NONOXYNOL-10; GLYCERIN; SODIUM HYDROXIDE; POTASSIUM IODIDE; WATER

Povidone Iodine Swabsticks

Active ingredient

Povidone-lodine USP10%

Purpose

Antiseptic

Use

for antiseptic skin preparation

Warnings

For external use only.

do not use

- if allergic to lodine
- do not use in the eyes

Stop use and ask a doctor if

- redness,irritation,swelling or pain persists or increases
- infection occurs

Keep out of reach of children.

In case of accidental ingestion,seek professional assistance or consult a poison control center immediately. Avoid pooling beneath patient.

Ask a doctor before use

if injuries are

- deep or puncture wounds
- serious burns

Directions

apply locally as needed

Other information

■1% titratable iodine ■For hospital or professional use only ■Store at room temperature. ■Avoid excessive heat. ■Not made with natural rubber latex.

Inactive ingredients:

Citric Acid,Alkyl Glucoside,Hydroxyethyl Cellulose,Nonoxynol-10,Glycerin,Sodium Hydroxide,Potassium lodide,Purified Water.